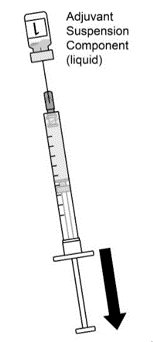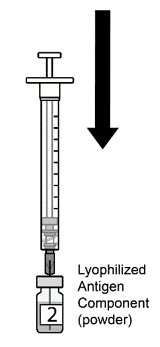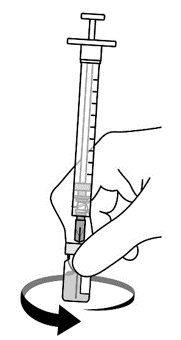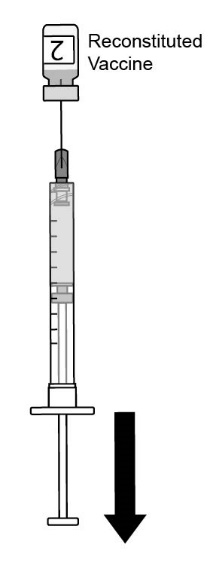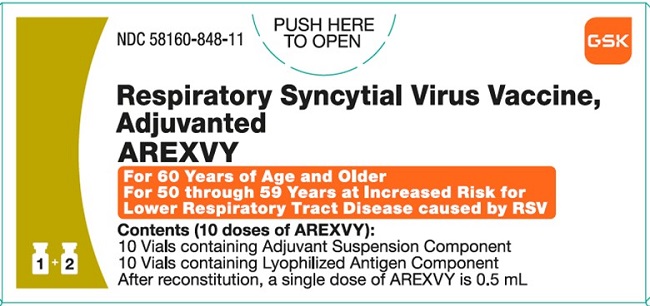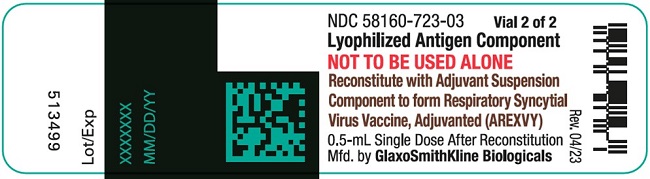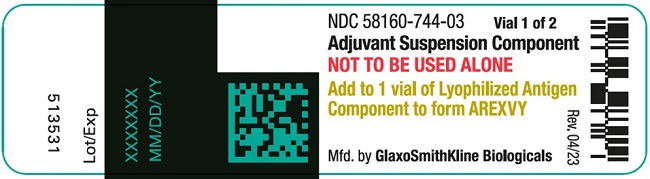 DRUG LABEL: Arexvy
NDC: 58160-848 | Form: KIT | Route: INTRAMUSCULAR
Manufacturer: GlaxoSmithKline Biologicals SA
Category: other | Type: VACCINE LABEL
Date: 20250808

ACTIVE INGREDIENTS: RECOMBINANT RESPIRATORY SYNCYTIAL VIRUS PRE-FUSION F PROTEIN ANTIGEN 120 ug/0.5 mL
INACTIVE INGREDIENTS: TREHALOSE DIHYDRATE; POLYSORBATE 80; MONOBASIC POTASSIUM PHOSPHATE; DIBASIC POTASSIUM PHOSPHATE; MONOPHOSPHORYL LIPID A TRIETHYLAMINE; QUILLAJA SAPONIN (QS-21); 1,2-DIOLEOYL-SN-GLYCERO-3-PHOSPHOCHOLINE; CHOLESTEROL; SODIUM CHLORIDE; SODIUM PHOSPHATE, DIBASIC, ANHYDROUS; MONOBASIC POTASSIUM PHOSPHATE; WATER

HIGHLIGHTS OF PRESCRIBING INFORMATION

These highlights do not include all the information needed to use AREXVY safely and effectively. See full prescribing information for AREXVY.
AREXVY (Respiratory Syncytial Virus Vaccine, Adjuvanted) for injectable suspension, for intramuscular use
Initial U.S. Approval: 2023

RECENT MAJOR CHANGES

Warnings and Precautions, Guillain-Barré Syndrome (5.1) | 1/2025

1 INDICATIONS AND USAGE

AREXVY is a vaccine indicated for active immunization for the prevention of lower respiratory tract disease (LRTD) caused by respiratory syncytial virus (RSV) in:

- individuals 60 years of age and older; (1)
- individuals 50 through 59 years of age who are at increased risk for LRTD caused by RSV. (1)

2 DOSAGE AND ADMINISTRATION

For intramuscular use.

AREXVY is administered as a single 0.5 mL dose (2.1)

3 DOSAGE FORMS AND STRENGTHS

For injectable suspension. AREXVY is supplied as a single-dose vial of lyophilized antigen component to be reconstituted with the accompanying vial of adjuvant suspension component. A single dose after reconstitution is 0.5 mL. (3)

4 CONTRAINDICATIONS

History of severe allergic reaction (e.g., anaphylaxis) to any component of the vaccine. (4)

5 WARNINGS AND PRECAUTIONS

The results of a postmarketing observational study suggest an increased risk of Guillain-Barré syndrome during the 42 days following vaccination with AREXVY. (5.1, 6.2)

6 ADVERSE REACTIONS

- The most commonly reported adverse reactions (≥10%), in individuals 60 years of age and older, were injection site pain (60.9%), fatigue (33.6%), myalgia (28.9%), headache (27.2%), and arthralgia (18.1%). (6.1)
- The most commonly reported adverse reactions (≥10%), in individuals 50 through 59 years of age, were injection site pain (75.8%), fatigue (39.8%), myalgia (35.6%), headache (31.7%), arthralgia (23.4%), erythema (13.2%), and swelling (10.4%). (6.1)

To report SUSPECTED ADVERSE REACTIONS, contact GlaxoSmithKline at 1-888-825-5249 or VAERS at 1-800-822-7967 or www.vaers.hhs.gov.

FULL PRESCRIBING INFORMATION

1 INDICATIONS AND USAGE

AREXVY is a vaccine indicated for active immunization for the prevention of lower respiratory tract disease (LRTD) caused by respiratory syncytial virus (RSV) in:

- individuals 60 years of age and older;
- individuals 50 through 59 years of age who are at increased risk for LRTD caused by RSV.

2 DOSAGE AND ADMINISTRATION

2.1 Dose and Schedule

Administer a single dose (0.5 mL) of AREXVY as an intramuscular injection.

2.2 Preparation

AREXVY is supplied in 2 vials that must be combined prior to administration. Prepare AREXVY by reconstituting the lyophilized antigen component (a sterile white powder) with the accompanying adjuvant suspension component (an opalescent, colorless to pale brownish sterile liquid). Use only the supplied adjuvant suspension component for reconstitution. The reconstituted vaccine should be an opalescent, colorless to pale brownish liquid. Parenteral drug products should be inspected visually for particulate matter and discoloration prior to administration, whenever solution and container permit. If either of these conditions exists, the vaccine should not be administered.

Figure 1. Cleanse both vial stoppers. Using a sterile needle and sterile syringe, withdraw the entire contents of the vial containing the adjuvant suspension component (liquid) by slightly tilting the vial. Vial 1 of 2.

Figure 2. Slowly transfer entire contents of syringe into the lyophilized antigen component vial (powder). Vial 2 of 2.

Figure 3. Gently swirl the vial until powder is completely dissolved. Do not shake vigorously.

Figure 4. After reconstitution, withdraw 0.5 mL from the vial containing the reconstituted vaccine and administer intramuscularly.

2.3 Administration

For intramuscular use.

After reconstitution, administer AREXVY immediately or store protected from light in the refrigerator between 2°C and 8°C (36°F to 46°F) or at room temperature [up to 25°C (77°F)] and use within 4 hours. Discard reconstituted vaccine if not used within 4 hours.

3 DOSAGE FORMS AND STRENGTHS

For injectable suspension. AREXVY is supplied as a single-dose vial of lyophilized antigen component to be reconstituted with the accompanying vial of adjuvant suspension component. A single dose after reconstitution is 0.5 mL.

4 CONTRAINDICATIONS

Do not administer AREXVY to anyone with a history of a severe allergic reaction (e.g., anaphylaxis) to any component of AREXVY [see Description (11)].

5 WARNINGS AND PRECAUTIONS

5.1 Guillain-Barré Syndrome

The results of a postmarketing observational study suggest an increased risk of Guillain-Barré syndrome during the 42 days following vaccination with AREXVY [see Adverse Reactions (6.2)].

5.2 Preventing and Managing Allergic Vaccine Reactions

Appropriate medical treatment must be immediately available to manage potential anaphylactic reactions following administration of AREXVY.

5.3 Syncope

Syncope (fainting) may occur in association with administration of injectable vaccines, including AREXVY. Procedures should be in place to avoid injury from fainting.

5.4 Altered Immunocompetence

Immunocompromised persons, including those receiving immunosuppressive therapy, may have a diminished immune response to AREXVY.

6 ADVERSE REACTIONS

In a clinical trial conducted in participants 60 years of age and older (NCT04886596), the most commonly reported adverse reactions (≥10%) were injection site pain (60.9%), fatigue (33.6%), myalgia (28.9%), headache (27.2%), and arthralgia (18.1%).

In a clinical trial conducted in participants 50 through 59 years of age (NCT05590403), the most commonly reported adverse reactions (≥10%) were injection site pain (75.8%), fatigue (39.8%), myalgia (35.6%), headache (31.7%), arthralgia (23.4%), erythema (13.2%), and swelling (10.4%).

6.1 Clinical Trials Experience

Because clinical trials are conducted under widely varying conditions, adverse reaction rates observed in the clinical trials of a vaccine cannot be directly compared with rates in the clinical trials of another vaccine and may not reflect the rates observed in practice.

Individuals 60 Years of Age and Older

The safety of AREXVY was evaluated in 17,879 vaccine recipients.

Study 1 (NCT04886596) is a placebo‑controlled, Phase 3 clinical study conducted in Europe, North America, Asia, and the Southern Hemisphere (South Africa, Australia, and New Zealand), involving 24,966 participants, 60 years of age and older, who received AREXVY (N = 12,467) or saline placebo (N = 12,499). Study 2 (NCT04732871) is a non–placebo-controlled, open‑label, Phase 3 clinical study conducted in Europe, North America, and Asia, involving 1,653 participants, 60 years of age and older, who received AREXVY. Study 3 (NCT04841577) is a non–placebo-controlled, open‑label, Phase 3 clinical study conducted in New Zealand, Panama, and South Africa, involving participants 60 years of age and older who received 1 dose of AREXVY and FLUARIX QUADRIVALENT concomitantly (N = 442) or sequentially (N = 443). Study 5 (NCT05559476) is a non–placebo-controlled, open‑label, clinical study conducted in the United States involving participants 65 years of age and older who received 1 dose of AREXVY and FLUZONE HIGH DOSE QUADRIVALENT (influenza vaccine, high dose; manufactured by Sanofi Pasteur, Inc.) concomitantly (N = 516) or sequentially (N = 513). Study 6 (NCT05568797) is a non–placebo-controlled, open‑label, clinical study conducted in Belgium, Finland, France, Spain, and the United Kingdom involving participants 65 years of age and older who received 1 dose of AREXVY and FLUAD QUADRIVALENT (influenza vaccine, adjuvanted; manufactured by Seqirus, Inc.) concomitantly (N = 523) or sequentially (N = 522).

At the time of vaccination in study 1, the median age of the population was 69.0 years; 13,943 (55.8%) participants were 60 to 69 years of age, 8,978 (36.0%) participants were 70 to 79 years of age, and 2,045 (8.2%) participants were 80 years of age and older. The majority of participants were White (79.4%), followed by Black (8.7%), Asian (7.6%), and other racial/ethnic groups (4.3%); 5.5% were of Hispanic or Latino ethnicity; 51.7% were female. In study 2, the median age of the population at the time of vaccination was 69.0 years; 820 (49.6%) participants were 60 to 69 years of age, 621 (37.6%) participants were 70 to 79 years of age, and 212 (12.8%) participants were 80 years of age and older. In study 2, the majority of participants were White (67.8%), followed by Asian (30.0%), Black (2.0%), and other racial/ethnic groups (0.2%); 1.9% were of Hispanic or Latino ethnicity; 54.6% were female. In study 3, the median age of the population at the time of the vaccination was 67.0 years; 519 (58.6%) participants were 60 to 69 years of age, 288 (32.5%) participants were 70 to 79 years of age, and 78 (8.8%) participants were 80 years of age and older, respectively. In study 3, the majority of the participants were of mixed race (50.3%), followed by White (30.7%), and Black (16.0%); 34.7% were of Hispanic or Latino ethnicity; 51.5% were female. In study 5, the median age of the population was 70 years. The majority of the participants were White (68.7%), followed by other racial groups (15.8%), Black (13.6%), American Indian or Alaskan Native (1.0%), and Asian (0.8%); 32.1% were of Hispanic or Latino ethnicity; 49.6% were female. In study 6, the median age of the population was 71 years. The majority of the participants were White (99.3%), followed by American Indian or Alaska Native (0.3%), Unknown Race (0.1%), Black (0.1%), Asian (0.1%), and Mixed Race (0.1%); 1.8% were of Hispanic or Latino ethnicity; 49.3% were female.

Safety Data from Study 1

Solicited Adverse Reactions: In study 1, a subset of study participants (solicited safety set) was monitored for solicited adverse reactions using standardized paper diary cards during the 4 days (i.e., day of vaccination and the next 3 days) following a dose of AREXVY or placebo; 879 participants received AREXVY and 878 participants received placebo. The other study participants did not prospectively record solicited reactions on a diary card but may have reported them as unsolicited adverse reactions.

The reported frequencies of specific solicited local (administration site) and systemic adverse reactions (per participant) are presented in Table 1.

Table 1. Percentage of Participants with Solicited Local Adverse Reactions and Systemic Adverse Reactions within 4 Days of Vaccination in Individuals 60 Years of Age and Older (Solicited Safety Set with 4-Day Diary Card)
 | AREXVY; % | Placeboa; %
Local Adverse Reactions | N = 879 | N = 874
Pain, Anyb | 60.9 | 9.3
Pain, Grade 3b | 1 | 0
Erythema, >20 mm | 7.5 | 0.8
Erythema, >100 mm | 0.2 | 0
Swelling, >20 mm | 5.5 | 0.6
Swelling, >100 mm | 0.2 | 0
Systemic Adverse Reactions | N = 879 | N = 878
Fatigue, Anyc | 33.6 | 16.1
Fatigue, Grade 3c | 1.7 | 0.5
Myalgia, Anyc | 28.9 | 8.2
Myalgia, Grade 3c | 1.4 | 0.3
Headache, Anyc | 27.2 | 12.6
Headache, Grade 3c | 1.3 | 0
Arthralgia, Anyc | 18.1 | 6.4
Arthralgia, Grade 3c | 1.3 | 0.6
Fever, ≥38.0°C/100.4°Fd | 2.0 | 0.3
Fever, >39.0°C/102.2°Fd | 0.1 | 0.1
N = Exposed set for solicited safety set included all participants with at least 1 documented dose and who completed their diary.
a Placebo was a saline solution.
b Any grade pain: Defined as any pain neither interfering with nor preventing normal everyday activities (Grade 1), painful when limb is moved and interferes with everyday activities (Grade 2), or significant pain at rest and prevents normal everyday activities (Grade 3).
c Any grade fatigue, myalgia, headache, arthralgia: Defined as event easily tolerated (Grade 1), interfering with normal activity (Grade 2), or preventing normal activity (Grade 3).
d Temperature taken by any route (oral, axillary, or tympanic).

In the solicited safety set, the local administration site adverse reactions reported with AREXVY had a median duration of 2 days, and the systemic adverse reactions reported with AREXVY had a median duration ranging between 1 and 2 days.

Unsolicited Adverse Events: In all participants from study 1, unsolicited adverse events were monitored using paper diary cards during the 30-day period following vaccination (day of vaccination and the next 29 days).

Among participants in the solicited safety set, (AREXVY, N = 879 or placebo, N = 878), unsolicited adverse events occurring within 30 days after vaccination were reported in 14.9% and 14.6% of participants who received AREXVY and placebo, respectively.

In the exposed set, 24,966 participants, 60 years of age and older, received at least 1 dose of AREXVY (N = 12,467) or placebo (N = 12,499). Unsolicited adverse events occurring within 30 days of vaccination were reported in 33.0% and 17.8% of participants, respectively. The higher frequency of reported unsolicited adverse events among participants who received AREXVY, compared to participants who received placebo, was primarily attributed to events that are consistent with adverse reactions solicited among participants in the reactogenicity subset. Within 30 days after vaccination, atrial fibrillation was reported in 10 participants who received AREXVY and 4 participants who received placebo (of which 7 events in AREXVY arm and 1 event in placebo arm were serious); the onset of symptoms ranged from 1 to 30 days post vaccination. The currently available information on the atrial fibrillation is insufficient to determine a causal relationship to the vaccine. There were no other notable patterns or numerical imbalances between groups for specific categories of unsolicited adverse events.

Serious Adverse Events: In study 1, participants were monitored for all serious adverse events (SAEs) that occurred during the 6‑month period following administration of AREXVY (N = 12,467) or placebo (N = 12,499).

SAEs with onset within 6 months following vaccination were reported at similar rates in participants who received AREXVY (4.2%) or placebo (4.0%). Serious events of atrial fibrillation were reported in 13 participants who received AREXVY and 15 participants who received placebo within 6 months after vaccination.

Deaths: In study 1, with a median follow-up time of 12.2 months post‑vaccination, adverse events leading to death were reported for 110 participants (0.9%) who received a single dose of AREXVY (N = 12,469) and for 114 participants (0.9%) who received placebo (N = 12,503). Based on available information, there is no evidence of causal relationship to AREXVY. Causes of death among participants were consistent with those generally reported in adult and elderly populations.

Potential Immune‑Mediated Diseases: In study 1, participants were monitored for all potential immune‑mediated diseases (pIMDs) that occurred during the 6‑month period following administration of AREXVY (N = 12,467) or placebo (N = 12,499).

New onset pIMDs or exacerbation of existing pIMDs within 6 months following vaccination were reported for 0.3% of participants who received AREXVY and 0.3% of participants who received placebo. There were no notable imbalances between study groups in individual pIMDs reported.

Serious Adverse Events Reported from Other Studies

Study 2: Guillain-Barré syndrome beginning 9 days after AREXVY vaccination was reported in a participant enrolled in a study site in Japan.

Study 3: Acute disseminated encephalomyelitis (ADEM) was reported in 2 participants enrolled in a study site in South Africa; the onset of the symptoms was 7 and 22 days post vaccination, respectively. One event was fatal and the other non-fatal. These participants received AREXVY concomitantly with FLUARIX QUADRIVALENT. For both events, magnetic resonance imaging and cerebrospinal fluid analyses were not performed.

Individuals 50 through 59 Years of Age

Study 4 (NCT05590403) was a Phase 3, observer‑blind, randomized, placebo‑controlled study conducted in Argentina, Canada, Germany, Japan, the Netherlands, Poland, Spain, and the U.S., in participants 50 through 59 years of age (N = 769 AREXVY; N = 383 saline placebo), including a subset of participants with stable chronic medical conditions associated with an increased risk for LRTD caused by RSV defined as chronic pulmonary disease, chronic cardiovascular disease, diabetes, chronic kidney or liver disease (N = 386 AREXVY; N = 191 saline placebo). The study also enrolled participants 60 years of age and older (N = 381 AREXVY) [see Clinical Studies (14.2)].

At the time of vaccination in study 4, the median age was 57 years for the entire study population and 55 years for the age group 50 through 59 years. The racial/ethnic and sex distribution of study participants were similar in the two age groups. The majority of participants were White (83.8%), followed by Asian (11.2%), Black (3.3%), and other racial/ethnic groups (1.7%); 14.3% were of Hispanic or Latino ethnicity; 52.1% were female.

In study 4, all participants were monitored for solicited adverse reactions during the 4 days following vaccination (i.e., day of vaccination and the next 3 days) and for unsolicited adverse events, during the 30-day period following vaccination (day of vaccination and the next 29 days), using standardized paper diary cards. Participants were monitored for all SAEs and for all pIMDs (serious and non-serious cases) that occurred during the 6-month period following vaccination. Among participants, 99.2% have completed at least 6 months of follow-up following vaccination.

Solicited Adverse Reactions: The reported frequencies of specific solicited, local (administration site), and systemic adverse reactions among participants 50 through 59 years of age are presented in Table 2.

Table 2. Percentage of Participants with Solicited Local Adverse Reactions and Systemic Adverse Reactions within 4 Days of Vaccination from Study 4 (Exposed Set)
 | AREXVY; 50 through 59 Years of Age; % | Placeboa; 50 through 59 Years of Age; %
Local Adverse Reactions | N = 756 | N = 379
Pain, Anyb | 75.8 | 12.1
Pain, Grade 3b | 3.4 | 0.3
Erythema, >20 mm | 13.2 | 0.5
Erythema, >100 mm | 0.5 | 0
Swelling, >20 mm | 10.4 | 0.8
Swelling, >100 mm | 0.1 | 0
Systemic Adverse Reactions | N = 756 | N = 380
Fatigue, Anyc | 39.8 | 18.2
Fatigue, Grade 3c | 2.8 | 0.8
Myalgia, Anyc | 35.6 | 9.7
Myalgia, Grade 3c | 2.5 | 0.5
Headache, Anyc | 31.7 | 16.8
Headache, Grade 3c | 2.6 | 1.1
Arthralgia, Anyc | 23.4 | 7.9
Arthralgia, Grade 3c | 1.7 | 0.8
Fever, ≥38.0°C/100.4°Fd | 3.2 | 1.1
Fever, >39.0°C/102.2°Fd | 0.1 | 0.5
N = Exposed set included all participants with at least 1 documented dose and with completed diary card.
a Placebo was a saline solution.
b Any grade pain: Defined as any pain neither interfering with nor preventing normal everyday activities (Grade 1), painful when limb is moved and interferes with everyday activities (Grade 2), or significant pain at rest and prevents normal everyday activities (Grade 3).
c Any grade fatigue, myalgia, headache, arthralgia: Defined as event easily tolerated (Grade 1), interfering with normal activity (Grade 2), or preventing normal activity (Grade 3).
d Temperature taken by any route (oral or axillary).

The rates of solicited local and systemic adverse reactions (Table 2) were similar in participants 50 through 59 years of age either with or without pre-defined, stable, chronic medical conditions associated with an increased risk for LRTD caused by RSV.

Overall, the median duration of solicited local adverse reactions and solicited systemic adverse reactions after AREXVY vaccination was 2-3 days and 1-2 days, respectively.

Unsolicited Adverse Events: Unsolicited adverse events within 30 days after vaccination were reported in 13.8% of participants, 50 through 59 years of age, who received AREXVY (N = 769) compared to 12.0% of participants who received placebo (N = 383). Within 30 days after vaccination, there were no cases of atrial fibrillation reported in participants 50 through 59 years of age.

Serious Adverse Events: In study 4, participants were monitored for all SAEs that occurred during the 6-month period following administration of AREXVY (N = 769) or placebo (N = 383). Among participants 50 through 59 years of age, SAEs with onset within 6 months post vaccination were reported in 2.3% of those who received AREXVY and 2.1% of those who received placebo.

Deaths: Among participants 50 through 59 years of age, adverse events leading to death within 12 months after vaccination were reported for 4 (0.5%) participants who received AREXVY (N = 769) and 1 (0.3%) participant who received placebo (N = 383). None of these deaths were considered causally related to AREXVY.

Potential Immune-Mediated Diseases: In study 4, participants were monitored for all pIMDs that occurred during the 6-month period following administration of AREXVY (N = 769) or placebo (N = 383). Among participants 50 through 59 years of age, new onset pIMDs or exacerbation of existing pIMDs with onset within 6 months post vaccination were reported in 0.5% of those who received AREXVY and 0.3% of those who received placebo. There were no notable imbalances between study groups in individual pIMDs reported.

6.2 Postmarketing Experience

The following adverse reactions have been identified from spontaneous reports during postmarketing use of AREXVY. Because these reactions are reported voluntarily from a population of uncertain size, it is not always possible to reliably estimate their frequency or establish a causal relationship to the vaccine.

Nervous System Disorders

Guillain-Barré Syndrome

Postmarketing Observational Study of the Risk of Guillain-Barré Syndrome following Vaccination with AREXVY

The association between vaccination with AREXVY and Guillain-Barré syndrome (GBS) was evaluated among Medicare beneficiaries 65 years of age and older. Using Medicare claims data, between May 2023 through July 2024, vaccinations with AREXVY were identified through Current Procedural Terminology (CPT)/Healthcare Common Procedure Coding System (HCPCS) codes and National Drug Codes, and potential cases of hospitalized GBS among recipients of AREXVY were identified through International Classification of Diseases (ICD) codes. GBS diagnoses in claims data were confirmed by medical record review when available.

The risk of GBS following vaccination with AREXVY was assessed in self-controlled case series analyses using a risk window of 1 to 42 days post-vaccination and a control window of 43 to 90 days post-vaccination. The analyses of all GBS cases based on claims data suggest an increased risk of GBS during the 42 days following vaccination with AREXVY, with an incidence rate ratio (GBS cases in the risk window/control window) of 2.46 (95% CI 1.19, 5.08) and an estimated 7 excess cases of GBS per million doses administered to individuals 65 years of age and older. The background risk of GBS in a study population influences the excess GBS case estimate and may differ between studies, precluding direct comparison to excess GBS case estimates from other vaccine studies or populations.

The analyses of GBS diagnoses in claims data were supported by analyses of GBS cases confirmed by medical record review and by analyses of GBS cases in individuals who received AREXVY alone, without other concomitantly administered vaccines. While the results of this observational study suggest an increased risk of GBS with AREXVY, available evidence is insufficient to establish a causal relationship.

8 USE IN SPECIFIC POPULATIONS

8.1 Pregnancy

Risk Summary

All pregnancies have a risk of birth defect, loss, or other adverse outcomes. In the U.S. general population, the estimated background risk of major birth defects and miscarriage in clinically recognized pregnancies is 2% to 4% and 15% to 20%, respectively.

AREXVY is not approved for use in persons <50 years of age.

In a clinical study that enrolled pregnant individuals who received an investigational unadjuvanted RSV vaccine that contained the same RSVPreF3 antigen as AREXVY, an increase in preterm births was observed compared to pregnant individuals who received placebo (sucrose reconstituted with saline).

A developmental and reproductive toxicology study was performed in female rabbits administered AREXVY prior to mating and during gestation (0.5 mL at each occasion). This study revealed no adverse effects on female fertility, embryo-fetal, pre-weaning and post-natal development (see Data).

Data

Human Data: There are no data on the use of AREXVY in pregnant individuals. In a randomized controlled clinical trial that enrolled pregnant individuals in a 2:1 ratio, 3,557 received an investigational unadjuvanted RSV vaccine that contained the same RSVPreF3 antigen as AREXVY and 1,771 received placebo (sucrose reconstituted with saline) at 24 to 34 weeks gestation. In the vaccine and placebo groups, 6.81% and 4.95% of preterm births were reported.

Animal Data: In a developmental toxicity study, female rabbits were administered AREXVY by intramuscular injection 28 and 14 days prior to mating, on gestation Days 3, 9, 16, and 24, and on lactation Day 7. The total dose was 0.5 mL on each occasion (a single human dose of AREXVY is 0.5 mL). No adverse effects on female fertility or pre-weaning development up to post-natal Day 35 were observed.

8.2 Lactation

Risk Summary

It is not known whether AREXVY is excreted in human milk. AREXVY is not approved for use in persons <50 years of age. No human or animal data are available to assess the effects of AREXVY on the breastfed infant or on milk production/excretion.

The developmental and health benefits of breastfeeding should be considered along with the mother’s clinical need for AREXVY and any potential adverse effects on the breastfed child from AREXVY or from the underlying maternal condition. For preventive vaccines, the underlying maternal condition is susceptibility to disease prevented by the vaccine.

8.4 Pediatric Use

Evidence from an animal model strongly suggests that AREXVY would be unsafe in individuals younger than 2 years of age because of an increased risk of enhanced respiratory disease. Safety and effectiveness in individuals 2 years through 17 years of age have not been established.

8.5 Geriatric Use

Of the total number of participants (N = 24,966) who received AREXVY or placebo in study 1 (NCT04886596), 13,943 (55.8%) were 60 to 69 years of age, 8,978 (36.0%) were 70 to 79 years of age, and 2,045 (8.2%) were 80 years of age and older [see Adverse Reactions (6.1), Clinical Studies (14.1)].

11 DESCRIPTION

AREXVY (Respiratory Syncytial Virus Vaccine, Adjuvanted) is a sterile injectable suspension for intramuscular use. The vaccine is supplied as a vial of lyophilized recombinant respiratory syncytial virus glycoprotein F stabilized in pre-fusion conformation (RSVPreF3) as the antigen component, which must be reconstituted at the time of use with the accompanying vial of AS01E adjuvant as the adjuvant suspension component.

The RSVPreF3 antigen is expressed by culturing genetically engineered Chinese Hamster Ovary cells in media containing no antibiotics or animal-derived proteins. The RSVPreF3 protein is purified by several chromatographic and filtration steps, formulated with excipients, filled into vials, and lyophilized.

The AS01E adjuvant is composed of 3‑O‑desacyl‑4’‑monophosphoryl lipid A (MPL) from Salmonella minnesota and QS-21, a saponin purified from plant extract Quillaja saponaria Molina, combined in a liposomal formulation. The liposomes are composed of dioleoyl phosphatidylcholine (DOPC) and cholesterol in a phosphate-buffered saline solution containing disodium phosphate anhydrous, potassium dihydrogen phosphate, sodium chloride, and water for injection.

After reconstitution, each 0.5 mL dose is formulated to contain 120 mcg of the recombinant RSVPreF3 antigen, 25 mcg of MPL, and 25 mcg of QS-21. Each dose also contains 14.7 mg of Trehalose, 4.4 mg of sodium chloride, 0.83 mg of potassium dihydrogen phosphate, 0.26 mg of dipotassium phosphate, 0.18 mg of polysorbate 80, 0.15 mg of disodium phosphate anhydrous, 0.5 mg of DOPC, and 0.125 mg of cholesterol.

AREXVY contains no preservative. Each dose may also contain residual amounts of host cell proteins (≤2.0%) and DNA (≤0.80 ng/mg) from the manufacturing process.

The vial stoppers are not made with natural rubber latex.

12 CLINICAL PHARMACOLOGY

12.1 Mechanism of Action

AREXVY induces an immune response against RSVpreF3 that protects against LRTD caused by RSV.

13 NONCLINICAL TOXICOLOGY

13.1 Carcinogenesis, Mutagenesis, Impairment of Fertility

AREXVY has not been evaluated for carcinogenic or mutagenic potential or for impairment of male fertility.

14 CLINICAL STUDIES

14.1 Efficacy in Individuals 60 Years of Age and Older

Efficacy of AREXVY against RSV‑associated LRTD in individuals 60 years of age and older was evaluated for up to 3 RSV seasons in study 1 (NCT04886596), a Phase 3, randomized, placebo‑controlled, observer‑blind clinical study conducted in 17 countries from Northern and Southern Hemispheres.

The study excluded participants who were immunocompromised. Participants with pre‑existing, chronic, stable disease such as diabetes, hypertension, or cardiac disease were allowed to participate in the study if considered by the investigator as medically stable at the time of vaccination.

The primary population for efficacy analysis (referred to as the modified exposed set), included individuals 60 years of age and older receiving 1 dose of AREXVY or placebo and who did not report an RSV‑confirmed acute respiratory illness [ARI] prior to Day 15 after vaccination.

The primary efficacy analysis over the first RSV season included 24,960 participants randomized equally to receive 1 dose of AREXVY (N = 12,466) or placebo (N = 12,494).

The efficacy analysis up to the end of the second RSV season included participants who received a single dose of AREXVY before Season 1 (N = 12,469); due to valid informed consent obtained from some participants initially excluded from the primary efficacy analysis, there is a higher number of participants in the end of Season 2 analysis. Pre‑Season 2, participants who received AREXVY were re‑randomized to receive placebo (N = 4,991) or a second dose of AREXVY (N = 4,966). Participants who received placebo before Season 1 (N = 12,498) received a second dose of placebo before Season 2 (N = 10,031). The efficacy analysis up to the end of the third RSV season included participants who received a single dose of AREXVY before Season 1 (N = 12,468); duplicate data from one participant was excluded from end of Season 3 analysis.

The participants were followed up to the end of the third RSV season (median follow‑up time 30.6 months).

Among study 1 participants in the modified exposed set for the analysis of efficacy over the first RSV season, 51.7% were female; 79.4% were White, 8.7% were Black, 7.6% were Asian, and 4.3% were of other racial/ethnic groups including American Indian or Alaska Native, Native Hawaiian or Other Pacific Islander; 5.5% were of Hispanic or Latino ethnicity. The median age of participants was 69.0 years.

At baseline, 39.3% of participants had at least one comorbidity of interest; 19.7% of participants had an underlying cardiorespiratory condition (chronic obstructive pulmonary disease, asthma, any chronic respiratory/pulmonary disease, or chronic heart failure) and 25.8% of participants had endocrine and metabolic conditions (diabetes, advanced liver or renal disease). Among participants in the modified exposed set for the analysis of efficacy over 2 and over 3 RSV seasons, demographic and baseline characteristics were similar to those in the modified exposed set for the analysis of efficacy over the first RSV season.

In study 1, confirmed RSV cases were determined by quantitative Reverse Transcription Polymerase Chain Reaction (qRT‑PCR) on a nasopharyngeal swab during all ARI episodes. ARI was defined by the presence of at least 2 respiratory symptoms/signs for at least 24 hours (nasal congestion, sore throat, lower respiratory symptoms/signs, as described below), or at least 1 respiratory symptom/sign plus 1 systemic symptom/sign (fever or feverishness, fatigue, body aches, headache, decreased appetite) for at least 24 hours. LRTD was defined based on the following criteria: the participant must have experienced at least 2 lower respiratory symptoms/signs, including at least 1 lower respiratory sign for at least 24 hours, or experienced at least 3 lower respiratory symptoms for at least 24 hours. Lower respiratory symptoms included: new or increased sputum, new or increased cough, new or increased dyspnea (shortness of breath). Lower respiratory signs included: new or increased wheezing, crackles/rhonchi, respiratory rate ≥20 respirations/min, low or decreased oxygen saturation (O2 saturation <95% or ≤90% if baseline is <95%), need for oxygen supplementation.

In study 1, a severe RSV-associated LRTD was defined as an RT-PCR confirmed RSV-associated LRTD with at least 2 lower respiratory signs, or preventing normal, everyday activities or requiring supportive therapy.

Efficacy against Respiratory Syncytial Virus-Associated Lower Respiratory Tract Disease over the First Respiratory Syncytial Virus Season

The primary objective was to demonstrate the efficacy of AREXVY in the prevention of a first episode of confirmed RSV-A and/or B associated LRTD during the first season.

Compared with placebo, AREXVY significantly reduced the risk of developing RSV-associated LRTD by 82.6% (96.95% CI [57.9, 94.1]) in participants 60 years of age and older, which met the pre-specified success criterion for the primary study objective (Table 3). The median duration of efficacy follow-up was 6.7 months.

Vaccine efficacy analyses by age subgroup and for participants with at least one comorbidity of interest are presented in Table 3.

The vaccine efficacy against RSV‑A–associated LRTD and RSV‑B–associated LRTD was 84.6% (95% CI [32.1, 98.3]) and 80.9% (95% CI [49.4, 94.3]), respectively.

Table 3. Efficacy Analyses over the First Respiratory Syncytial Virus Season: First Respiratory Syncytial Virus-Associated Lower Respiratory Tract Disease Overall, by Age and Comorbidity Subgroups in Study 1a (Modified Exposed Set)
Subgroup | AREXVY |  |  | Placebo |  |  | % Efficacy; (CI)b
Subgroup | N | n | Incidence Rate per 1,000 Person-Years | N | n | Incidence Rate per 1,000 Person-Years | % Efficacy; (CI)b
Overall (≥60 years) | 12,466 | 7 | 1.0 | 12,494 | 40 | 5.8 | 82.6 (57.9, 94.1)
60 to 69 years | 6,963 | 4 | 1.0 | 6,979 | 21 | 5.5 | 81.0 (43.6, 95.3)
70 to 79 years | 4,487 | 1 | 0.4 | 4,487 | 16 | 6.5 | 93.8 (60.2, 99.9)
≥80 years | 1,016 | 2 | 3.6 | 1,028 | 3 | 5.4 | 33.8 (-477.7, 94.5)c
Participants with at least 1 comorbidity of interest | 4,937 | 1 | 0.4 | 4,861 | 18 | 6.6 | 94.6 (65.9, 99.9)
Two-sided exact CI for vaccine efficacy is derived based on Poisson model adjusted by age categories and regions.
N = Number of participants included in each group.
n = Number of participants having first occurrence of RSV-confirmed LRTD occurring from Day 15 post-vaccination.
a Study 1: NCT04886596.
b CI = Confidence Interval (96.95% for the overall ≥60 years and 95% for all subgroup analyses).
c Vaccine Efficacy (VE) for ≥80 years cannot be reliably estimated due to the low number of cases accrued in this age group.

Compared with placebo, AREXVY significantly reduced the risk of developing RSV-associated LRTD by 84.4% (95% CI [46.9, 97.0]) in participants 70 years of age and older.

Compared with placebo, AREXVY significantly reduced the risk of developing severe RSV-associated LRTD by 94.1% (95% CI [62.4, 99.9]) in participants 60 years of age and older. One case of severe RSV-associated LRTD in the group that received AREXVY and 17 cases in the group that received placebo were reported, amongst which 2 cases required supportive therapy i.e., oxygen supplementation.

Efficacy against Respiratory Syncytial Virus‑Associated Lower Respiratory Tract Disease over 2 and over 3 Respiratory Syncytial Virus Seasons

Participants 60 years of age and older who received 1 dose of AREXVY or placebo were followed over 3 RSV seasons (up to the end of the second and third seasons in the Northern Hemisphere), with a median follow‑up time of 17.8 months over 2 RSV seasons and 30.6 months over 3 RSV seasons. The vaccine efficacy against RSV‑associated LRTD over 2 RSV seasons was 67.2% (97.5% CI [48.2, 80.0]) and over 3 RSV seasons was 62.9% (97.5% CI [46.7, 74.8]).

The vaccine efficacy against RSV-A‑associated LRTD and RSV-B‑associated LRTD over 3 RSV seasons was 69.8% (97.5% CI [42.2, 85.7]) and 58.6% (97.5% CI [35.9, 74.1]), respectively.

Vaccine efficacy analyses by age subgroup and for participants with at least one comorbidity of interest are presented in Table 4.

Table 4. Efficacy Analyses over 2 and over 3 Respiratory Syncytial Virus Seasons: First Respiratory Syncytial Virus-Associated Lower Respiratory Tract Disease Overall, by Age and Comorbidity Subgroups in Study 1a (Modified Exposed Set)
Subgroup | AREXVYb |  |  | Placebo |  |  | % Efficacyc; (CI)d
Subgroup | N | n | Incidence Rate per 1,000 Person-Years | N | n | Incidence Rate per 1,000 Person-Years | % Efficacyc; (CI)d
Over 2 RSV Seasons
Overall (≥60 years) | 12,469 | 30 | 2.0 | 12,498 | 139 | 8.0 | 67.2 (48.2, 80.0)
60 to 69 years | 6,963 | 17 | 2.1 | 6,981 | 74 | 7.7 | 65.4 (40.4, 80.9)
70 to 79 years | 4,489 | 9 | 1.7 | 4,489 | 55 | 8.8 | 74.9 (48.4, 89.2)
≥80 years | 1,017 | 4 | 3.5 | 1,028 | 10 | 7.2 | 38.4 (-118.2, 86.1)e
Participants with at least 1 comorbidity of interest | 4,983 | 16 | 2.7 | 4,919 | 72 | 10.6 | 66.7 (41.8, 82.0)
Over 3 RSV Seasons
Overall (≥60 years) | 12,468 | 48 | 2.4 | 12,498 | 215 | 7.9 | 62.9 (46.7, 74.8)
60 to 69 years | 6,962 | 28 | 2.5 | 6,981 | 117 | 7.6 | 60.3 (39.5, 74.8)
70 to 79 years | 4,489 | 15 | 2.1 | 4,489 | 85 | 8.6 | 70.6 (48.4, 84.3)
≥80 years | 1,017 | 5 | 3.3 | 1,028 | 13 | 6.0 | 36.2 (-94.0, 82.5)e
Participants with at least 1 comorbidity of interest | 5,014 | 25 | 3.2 | 4,951 | 116 | 10.8 | 64.7 (45.1, 78.1)
Two‑sided exact CI for vaccine efficacy is derived based on Poisson model adjusted by age categories, regions and season.
N = Number of participants included in each group.
n = Number of participants having first occurrence of RSV‑confirmed LRTD occurring from Day 15 post‑vaccination.
a Study 1: NCT04886596.
b Participants who received a second dose of AREXVY did not contribute to these efficacy analyses after receipt of Dose 2.
c VE(%) Poisson method – adjusted by age, region, and season for overall (≥60 years) and participants with at least 1 comorbidity of interest; and adjusted by region and season for analysis by age category.
d CI = Confidence Interval (97.5% for the overall ≥60 years and 95% for all subgroup analyses).
e VE for ≥80 years cannot be reliably estimated due to the low number of cases accrued in this age group.

In participants 70 years of age and older, over 2 RSV seasons and over 3 RSV seasons, the vaccine efficacy against RSV‑associated LRTD was 69.3% (95% CI [43.4, 84.6]) and 66.0% (95% CI [44.3, 80.2]), respectively.

The vaccine efficacy against severe RSV‑associated LRTD over 2 RSV seasons was 78.8% (95% CI [52.6, 92.0]) in participants 60 years of age and older (7 cases in participants who received 1 dose of AREXVY and 48 cases in participants who received placebo, amongst which supportive therapy (i.e., oxygen supplementation and positive airway pressure) was required for 1 case in participants who received 1 dose of AREXVY and 5 cases in participants who received placebo). The vaccine efficacy against severe RSV‑associated LRTD over 3 RSV seasons was 67.4% (95% CI [42.4, 82.7]) in participants 60 years of age and older (15 cases in participants who received 1 dose of AREXVY and 75 cases in participants who received placebo, amongst which supportive therapy (i.e., oxygen supplementation and positive airway pressure) was required for 2 cases in participants who received 1 dose of AREXVY and 5 cases in participants who received placebo).

Efficacy against Respiratory Syncytial Virus‑Associated Lower Respiratory Tract Disease over the Second Respiratory Syncytial Virus Season and over the Third Respiratory Syncytial Virus Season

The vaccine efficacy against RSV‑associated LRTD over the second RSV season with median follow‑up of 6.3 months was 56.1% (95% CI [28.2, 74.4]) in participants 60 years of age and older (20 cases among participants who received 1 dose of AREXVY and 91 cases among participants who received placebo).

The vaccine efficacy against RSV‑associated LRTD over the third RSV season with median follow‑up of 7 months was 48.0% (95% CI [8.7, 72.0]) in participants 60 years of age and older (16 cases among participants who received 1 dose of AREXVY and 61 cases among participants who received placebo).

14.2 Immunogenicity in Individuals 50 through 59 Years of Age at Increased Risk for LRTD caused by RSV

In study 4, individuals 50 through 59 years of age with an increased risk of LRTD caused by RSV due to certain chronic medical conditions (chronic pulmonary disease, chronic cardiovascular disease, diabetes, chronic kidney or liver disease) were randomized to receive AREXVY (N = 386) or saline placebo (N = 191). A comparator group of individuals 60 years and older also received AREXVY (N = 381) [see Adverse Reactions (6.1)].

Effectiveness of AREXVY in individuals 50 through 59 years of age with chronic medical conditions was assessed by a comparison of RSV neutralizing antibody responses induced by AREXVY in this age group to antibody responses of individuals 60 years of age and older. The neutralizing antibody responses to RSV-A and RSV-B subtypes in individuals 50 through 59 years of age with chronic medical conditions met the criteria for immunobridging, as the upper limit (UL) of the 2-sided 95% CI for the Geometric Mean Titer (GMT) ratio (GMT for individuals 60 years and older/GMT for individuals 50 through 59 years of age with chronic medical conditions) was ≤1.50 and the UL of the 2-sided 95% CIs for seroresponse rate (SRR) difference (SRR for individuals 60 years and older minus SRR for individuals 50 through 59 years of age with chronic medical conditions) was ≤10% for the RSV-A and RSV-B subtypes (see Table 5).

Table 5. Adjusted Geometric Mean Titer (GMT) Values, Adjusted GMT Ratios, Seroresponse Rate (SRR) Values and SRR Difference in Terms of RSV-A and RSV-B Neutralizing Titers (ED60) in Individuals 50 through 59 Years of Age with Stable Chronic Medical Conditionsa Compared to Individuals 60 Years of Age and Older – Per Protocol Set
RSV-A Neutralizing Titers (ED60)
 | Adjusted GMTb; (95% CI) | Adjusted GMT Ratiob; (95% CI)c | SRR; %; (95% CI) | SRR Difference; %; (95% CI)d
Individuals 60 years of age and older; (N = 342) | 7,440.1; (6,768.4, 8,178.5) |  | 80.4; (75.8, 84.5)
Individuals 50 through 59 years of age with chronic medical conditions; (N = 343) | 8,922.7; (8,118.2, 9,806.9) | 0.8; (0.7, 1.0) | 86.9; (82.8, 90.3) | -6.5; (-12.1, -0.9)
RSV-B Neutralizing Titers (ED60)
 | Adjusted GMTb; (95% CI) | Adjusted GMT Ratiob; (95% CI)c | SRR; %; (95% CI) | SRR Difference; %; (95% CI)d
Individuals 60 years of age and older; (N = 341) | 8,062.8; (7,395.9, 8,789.9) |  | 74.5; (69.5, 79.0)
Individuals 50 through 59 years of age with chronic medical conditions; (N = 343) | 10,054.7; (9,225.4, 10,958.7) | 0.8; (0.7, 0.9) | 81.6; (77.1, 85.6) | -7.2; (-13.3, -0.9)
ED60: Estimated Dilution 60; CI = Confidence Interval; GMT = Geometric Mean Titer; SRR = Seroresponse Rate (The SRR was defined as the percentage of participants having a fold increase in neutralization titers ≥4 at 1 month post-study intervention administration over pre-study intervention administration).
N = Number of participants with both pre- and post-vaccination results available.
a Stable chronic medical conditions were those associated with an increased risk for LRTD caused by RSV defined as chronic pulmonary disease, chronic cardiovascular disease, diabetes, chronic kidney or liver disease.
b Comparison is done using the group ratio of adjusted GMT (individuals 60 years of age and older/individuals 50 through 59 years of age with chronic medical conditions) (ANCOVA model applied to the logarithm 10 transformed titers). The ANCOVA model included the group as fixed effects and the pre-dose logarithm 10 titer as covariate.
c,d The prespecified criteria for non-inferiority of the immune responses were defined as the 2-sided 95% CI upper limits (UL) on the adjusted GMT ratios (GMT for individuals 60 years and older/GMT for individuals 50 through 59 years of age with chronic medical conditions) ≤1.5 and the UL of the 2-sided 95% CI on the SRR difference (SRR for individuals 60 years and older minus SRR for individuals 50 through 59 years of age with chronic medical conditions) ≤10%.

14.3 Concomitant Administration

Concomitant Administration with Influenza Vaccines

In 3 open-label clinical studies, participants were randomized 1:1 to receive 1 dose of AREXVY administered either concomitantly at Month 0 or sequentially 1 month apart (referred to as the control group) with FLUARIX QUADRIVALENT in study 3 (N = 885), FLUZONE HIGH DOSE QUADRIVALENT in study 5 (N = 1,029), or FLUAD QUADRIVALENT (N = 1,045) in study 6 [see Adverse Reactions (6)].

In studies 3 and 5, the prespecified criteria for non-inferiority of the immune responses in the concomitant administration group versus the control group were met [upper limit of the 2-sided 95% confidence interval on the group GMT ratios ≤1.50 (control group/concomitant group)] for the RSV-A neutralizing titers (studies 3 and 5), the RSV-B neutralizing titers (study 5), and for the haemagglutinin inhibition (HI) titers against influenza strains A/Hong Kong/H3N2, A/Victoria/H1N1, B/Phuket/Yamagata and B/Washington/Victoria (study 3) and influenza strains A/Victoria/H1N1, A/Darwin/H3N2, B/Austria/Victoria and B/Phuket/Yamagata (study 5).

In study 6, the prespecified criteria for non-inferiority of the immune responses in the concomitant administration group versus the control group were met [upper limit of the 2-sided 95% confidence interval on the group GMT ratios ≤1.50 (control group/concomitant group)] for the RSV-A neutralizing titers and for HI titers against 3 of 4 influenza vaccine strains (A/Victoria/H1N1, B/Austria/Victoria, and B/Phuket/Yamagata); the noninferiority criterion was not met for HI titers against A/Darwin/H3N2 influenza strain, with the upper limit of the 95% CI of the GMT ratio of 1.53. In a post-hoc descriptive analysis, the GMT ratio [control group/concomitant group] was 1.16 [2-sided 95% CI (1.03, 1.30)] for RSV-B neutralizing titers.

16 HOW SUPPLIED/STORAGE AND HANDLING

AREXVY is supplied as 2 components: A single-dose vial of lyophilized antigen component (powder) and a single-dose vial of adjuvant suspension component (liquid) (packaged without syringes or needles).

Table 6: Product Presentation for AREXVY
Presentation | Carton NDC Number | Components
Presentation | Carton NDC Number | Adjuvant Suspension Component (liquid) | Lyophilized Antigen Component (powder)
Outer carton of 10 doses | 58160-848-11 | 10 vials; NDC 58160-744-03 | 10 vials; NDC 58160-723-03

16.1 Storage before Reconstitution

Adjuvant suspension component vials: Store refrigerated between 2°C and 8°C (36°F and 46°F). Store in the original package in order to protect vials from light. Do not freeze. Discard if the adjuvant suspension component has been frozen.

Lyophilized antigen component vials: Store refrigerated between 2°C and 8°C (36°F and 46°F). Store in the original package in order to protect vials from light. Do not freeze. Discard if the antigen component has been frozen.

16.2 Storage after Reconstitution

- Administer immediately or store in the refrigerator between 2°C and 8°C (36°F to 46°F) or at room temperature [up to 25°C (77°F)] for up to 4 hours prior to use.
- Protect vials from light.
- Discard reconstituted vaccine if not used within 4 hours.
- Do not freeze. Discard if the vaccine has been frozen.

17 PATIENT COUNSELING INFORMATION

- Inform vaccine recipients of the potential benefits and risks of vaccination with AREXVY.
- Inform vaccine recipients about the potential for adverse reactions that have been observed following administration of AREXVY.
- Provide the Vaccine Information Statements, which are available free of charge at the Centers for Disease Control and Prevention (CDC) website (www.cdc.gov/vaccines).

AREXVY and FLUARIX QUADRIVALENT are owned by or licensed to the GSK group of companies. The other brands listed are trademarks owned by or licensed to their respective owners and are not owned by or licensed to the GSK group of companies. The makers of these brands are not affiliated with and do not endorse the GSK group of companies or its products.

Manufactured by GlaxoSmithKline Biologicals
Rixensart, Belgium, U.S. License 1617, and
Distributed by GlaxoSmithKline
Durham, NC 27701

©2025 GSK group of companies or its licensor.
ARV:6PI

PACKAGE LABEL

PRINCIPAL DISPLAY PANEL

NDC 58160-848-11

AREXVY

Respiratory Syncytial Virus Vaccine, Adjuvanted

For 60 Years of Age and Older

For 50 through 59 Years at Increased Risk for Lower Respiratory Tract Disease caused by RSV

Contents (10 doses of AREXVY):

10 Vials containing Adjuvant Suspension Component

10 Vials containing Lyophilized Antigen Component

After reconstitution, a single dose of AREXVY is 0.5 mL

GSK

Adjuvant Made in Belgium. Antigen Made in Belgium and France

©2024 GSK group of companies or its licensor.

Rev. 07/24

520591

PACKAGE LABEL

PRINCIPAL DISPLAY PANEL (Antigen)

NDC 58160-723-03

Lyophilized Antigen Component

Vial 2 of 2

NOT TO BE USED ALONE

Reconstitute with Adjuvant Suspension Component to form Respiratory Syncytial Virus Vaccine, Adjuvanted (AREXVY)

0.5-mL Single Dose After Reconstitution

Mfd. By GlaxoSmithKline Biologicals

Rev 04/23

513499

PACKAGE LABEL

PRINCIPAL DISPLAY PANEL (Antigen)

NDC 58160-744-03

Adjuvant Suspension Component

Vial 1 of 2

NOT TO BE USED ALONE

Add to 1 vial of Lyophilized Antigen Component to form Arexvy

Mft. By GlaxoSmithKline Biologicals

Rev 04/23

513531